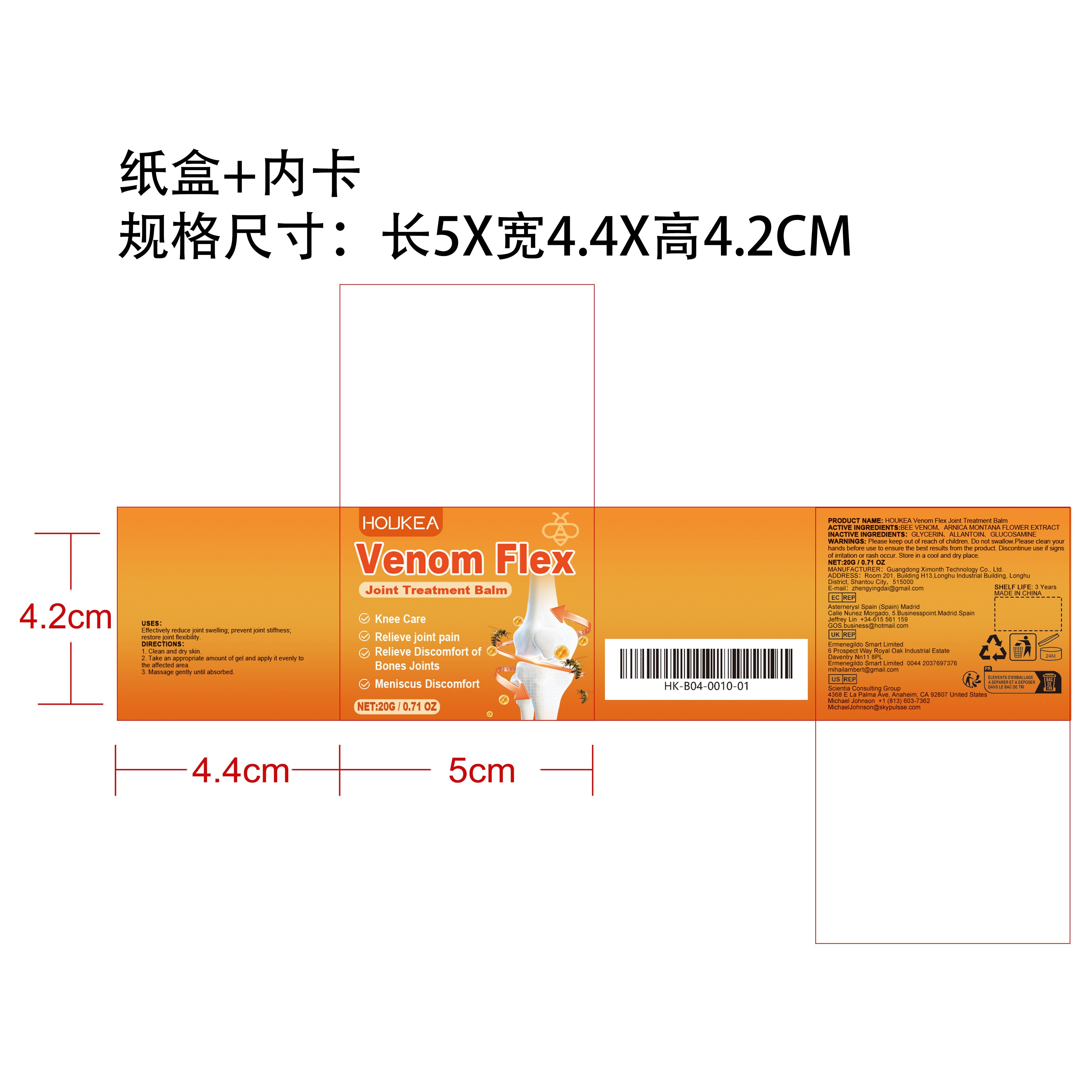 DRUG LABEL: HOUKEA Venom Flex Joint Treatment Balm
NDC: 84660-085 | Form: CREAM
Manufacturer: Guangdong Ximonth Technology Co., Ltd.
Category: otc | Type: HUMAN OTC DRUG LABEL
Date: 20241028

ACTIVE INGREDIENTS: ARNICA MONTANA FLOWER 2 g/20 g; APIS MELLIFERA VENOM 6 g/20 g
INACTIVE INGREDIENTS: GLUCOSAMINE 6 g/20 g; GLYCERIN 3 g/20 g; ALLANTOIN 3 g/20 g

ACTIVE INGREDIENTS

APIS MELLIFERA VENOM，ARNICA MONTANA FLOWER

PURPOSE

Effectively reduce joint swelling; prevent joint stiffness; restore joint flexibility.

USES

1. Clean and dry skin.2. Take an appropriate amount of gel and apply it evenly to the affected area.3. Massage gently until absorbed.

WARNINGS

Please keep out of reach of children. Do not swallow.Please clean your hands before use to ensure the best results from the product. Discontinue use if signs of irritation or rash occur. Store in a cool and dry place.

STOP USE

Discontinue use if signs of irritation or rash occur.

DO NOT USE

Discontinue use if signs of irritation or rash occur.

KEEP OUT OF REACH OF CHILDREN

Please keep out of reach of children. Do not swallow.

STORAGE AND HANDLING

Store in a cool and dry place.

INACTIVE INGREDIENT

GLYCERIN、ALLANTOIN、GLUCOSAMINE